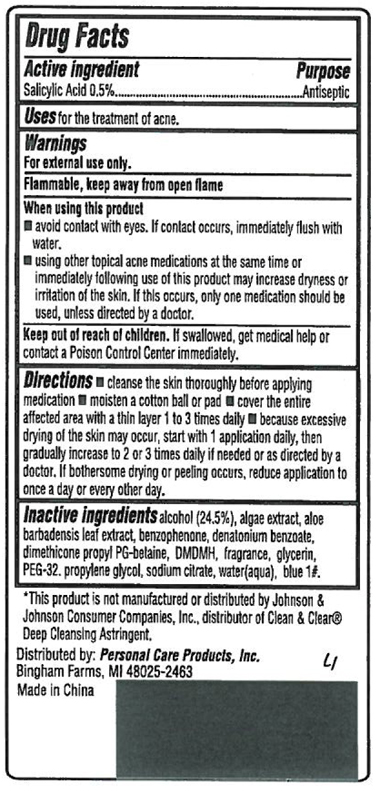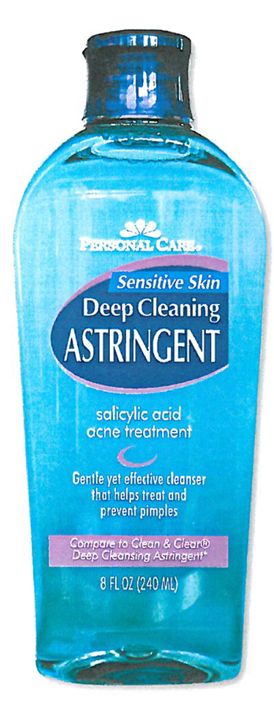 DRUG LABEL: Sensitive Skin Deep Cleaning Astringent
                        
NDC: 29500-0240 | Form: LIQUID
Manufacturer: Personal Care Productrs
Category: otc | Type: HUMAN OTC DRUG LABEL
Date: 20111230

ACTIVE INGREDIENTS: SALICYLIC ACID 0.5 mL/100 mL
INACTIVE INGREDIENTS: ALCOHOL 24.5 mL/100 mL; ALOE VERA FLOWER; BENZOPHENONE; GLYCERIN; PROPYLENE GLYCOL; SODIUM CITRATE; WATER

Personal Care Sensitive Skin Deep Cleaning Astringent

Drug Facts

Active Ingredient Purpose

Salicylic Acid 0.5%..............................Antiseptic

PURPOSE

Uses: for the treatment of acne.

WARNINGS

For external use only.

Flammable, keep away from open flame

INDICATIONS AND USAGE

Uses: For the treatment of acne

Keep out of reach of children. If swallowed, get medical help of contact a Poison Control Center immediately.

Directions:

Cleanse the skin thoroughly before applying medication

moisten a cotton ball or pad

cover the entire affected rea with a thin layer 1 to 3 times daily, then gradually increase to 2 or 3 times daily if needed or as directed by a doctor. If bothersome drying or peeling occurs, reudce application to once a day or every other day.

Inactive Ingredients

alcohol (24.5%), algae extract, aloe barbadensis leaf extract, benzophenone, denalonium benzoate, dimethicone propyl PG-belaine, DMDMH, fragrance, glycerine, PEG-32, propylene glycol, sodium citrate, water (aqua), blue #1

*This product is not manufactured or distributed by Johnson and Johnson Consumer Companies, Inc. distributor of Clean and Clear(r) Deep Cleaning Astringent

Distributed by Personal Care Products, Inc.

Bingham Farms, MI 48025-2463

Made in China

PACKAGE LABEL

Personal Care

Sensitive Skin

Deep Cleaning Astringent

salicylic acid

acne treatment

Gentle yet effective cleanser

that helps treat and prevent pimples

Compare to Clean and Clear (r)

Deep Cleansing Astringent

8 FL OZ (240 ML)